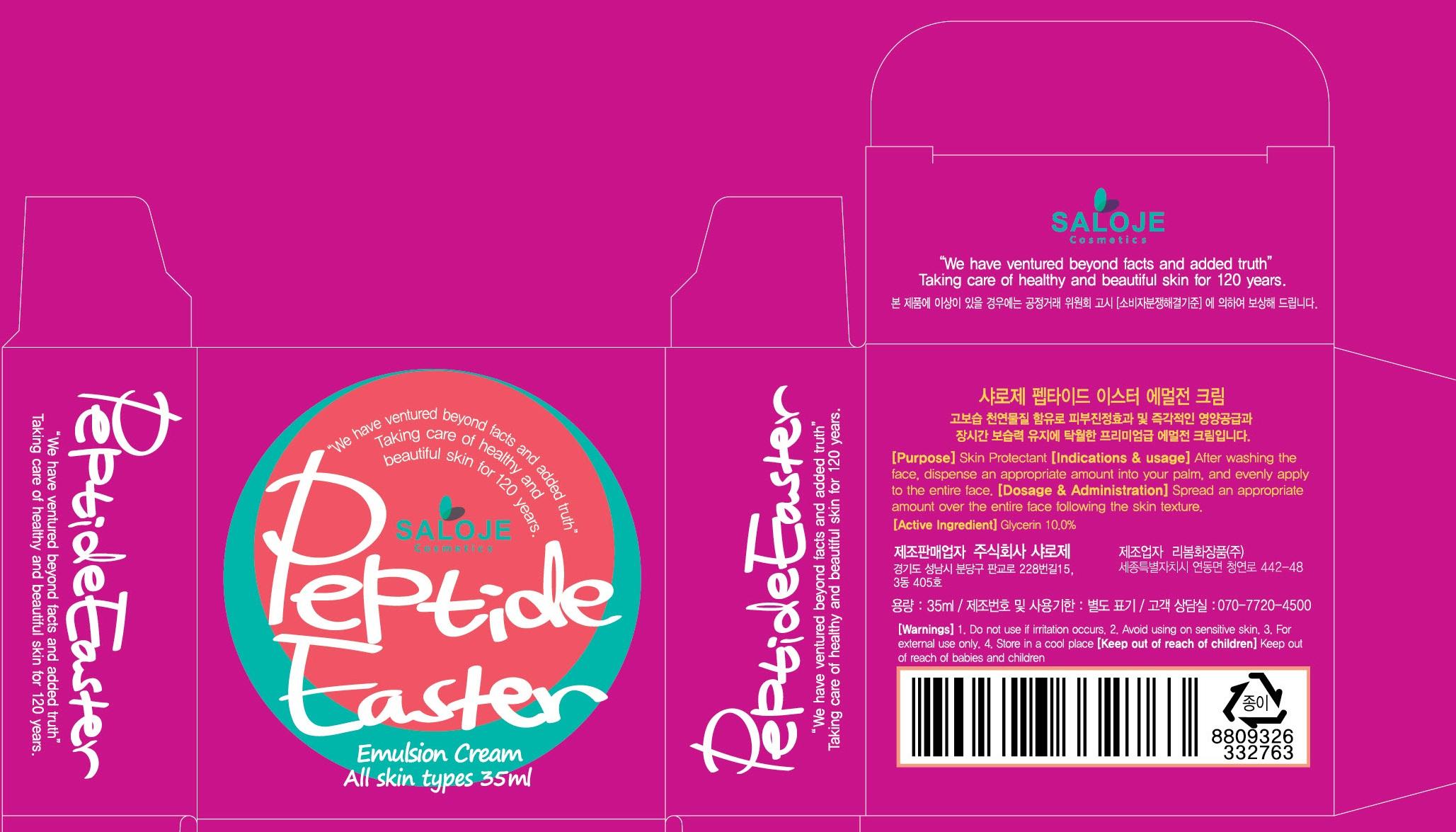 DRUG LABEL: Peptide Easter
NDC: 70141-030 | Form: EMULSION
Manufacturer: SALOJE Inc
Category: otc | Type: HUMAN OTC DRUG LABEL
Date: 20151015

ACTIVE INGREDIENTS: Glycerin 3.5 mg/35 mL
INACTIVE INGREDIENTS: Water; Butylene Glycol

ACTIVE INGREDIENT

Active Ingredient: Glycerin 10.0%

INACTIVE INGREDIENT

Inactive Ingredients: Water, Butylene Glycol, Caprylic/Capric Triglyceride, Betaine, Cetearyl Alcohol, Butylene Glycol Dicaprylate/Dicaprate, Squalane, Sorbitan Stearate, Stearic Acid, Polyglyceryl-10 Distearate, Glyceryl Stearate, Dimethicone, Sodium Hyaluronate, Aureobasidium Pullulans Ferment Filtrate, Tocopheryl Acetate, Portulaca Oleracea Extract, Aloe Barbadensis Leaf Juice, Rehmannia Chinensis Root Extract, Schizonepeta Tenuifolia Extract, Saururus Chinensis Leaf/Root Extract, Polygonum Fagopyrum (Buckwheat) SeedExtract, Glycine Max (Soybean) Seed Extract, Acanthopanax Senticosus (Eleuthero) RootExtract, Ulmus Davidiana Root Extract, Poria Cocos Extract, Ginkgo Biloba Leaf Extract, Prunus Armeniaca (Apricot) Kernel Extract, Sanguisorba Officinalis Root Extract, Phellodendron Amurense Bark Extract, Prunus Mume Fruit Extract, Zanthoxylum Piperitum Fruit Extract, Pinus Densiflora Extract, Magnolia Obovata Bark Extract, Polygonum Cuspidatum Root Extract, Sophora Angustifolia Root Extract, Camellia Sinensis Leaf Extract, Ganoderma Lucidum (Mushroom) Stem Extract, Carthamus Tinctorius (Safflower) Flower Extract, Oryza Sativa (Rice) Bran Extract, Bletia Hyacinthina Bulb Extract, Allantoin, 1,2-Hexanediol, Propanediol, Caprylyl Glycol, Illicium Verum (Anise) Fruit Extract, Arginine, Carbomer, Fragrance, Alloferon-1

PURPOSE

Purpose: Skin Protectant

WARNINGS

Warnings: 1. Do not use if irritation occurs. 2. Avoid using on sensitive skin. 3. For external use only. 4. Store in a cool place

Keep out of reach of children: Keep out of reach of babies and children

INDICATIONS & USAGE

Indications & usage: After washing the face, dispense an appropriate amount into your palm, and evenly apply to the entire face.

DOSAGE & ADMINISTRATION

Dosage & Administration: Spread an appropriate amount over the entire face following the skin texture.